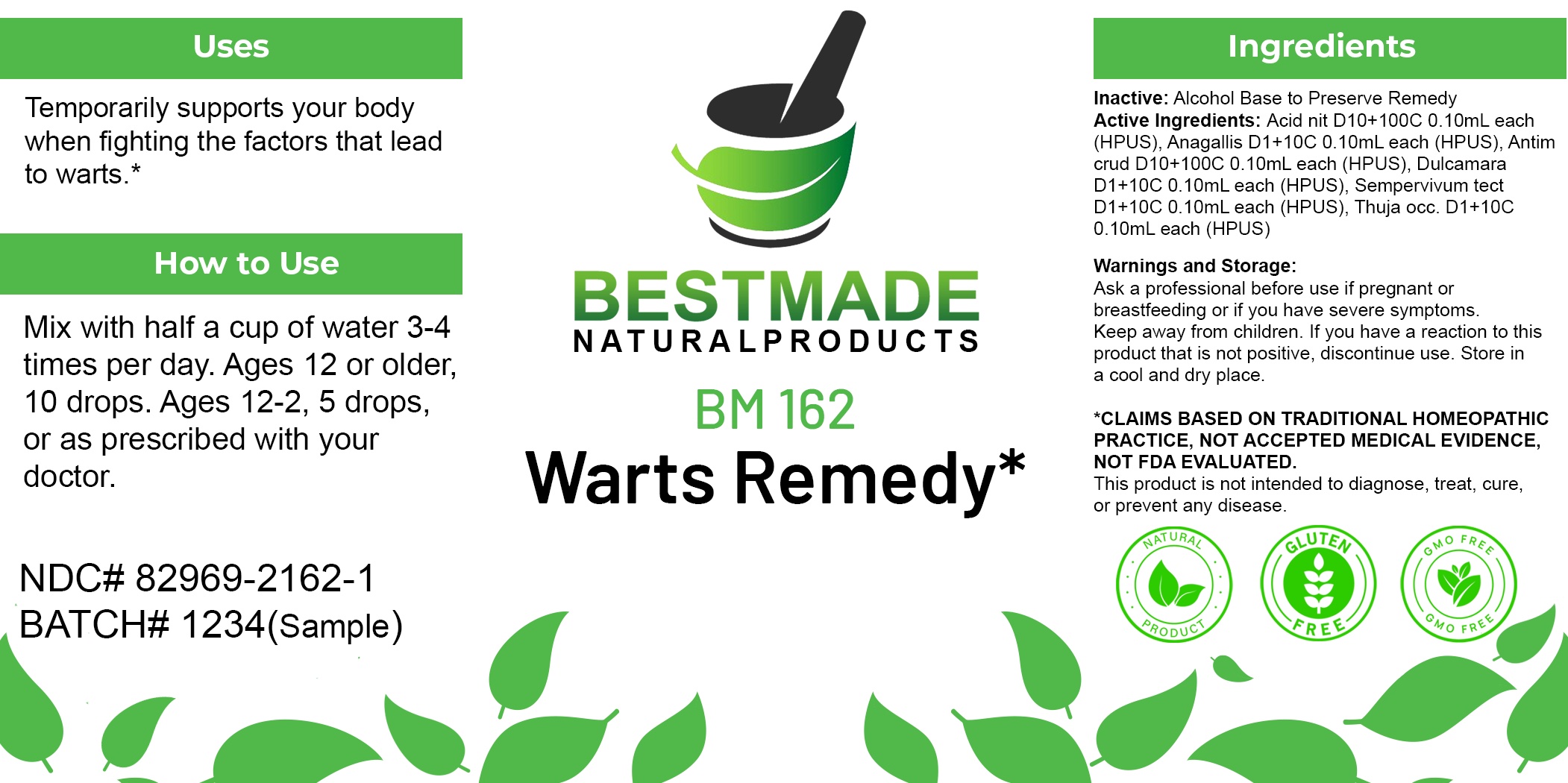 DRUG LABEL: Bestmade Natural Products BM162
NDC: 82969-2162 | Form: LIQUID
Manufacturer: Bestmade Natural Products
Category: homeopathic | Type: HUMAN OTC DRUG LABEL
Date: 20250403

ACTIVE INGREDIENTS: ANAGALLIS ARVENSIS WHOLE 30 [hp_C]/30 [hp_C]; SOLANUM DULCAMARA TOP 30 [hp_C]/30 [hp_C]; THUJA OCCIDENTALIS LEAFY TWIG 30 [hp_C]/30 [hp_C]; ANTIMONY TRISULFIDE 30 [hp_C]/30 [hp_C]; SEMPERVIVUM TECTORUM LEAF 30 [hp_C]/30 [hp_C]; NITRIC ACID 30 [hp_C]/30 [hp_C]
INACTIVE INGREDIENTS: ALCOHOL 30 [hp_C]/30 [hp_C]

BM162

DOSAGE AND ADMINISTRATION

How to Use

Mix with half a cup of water 3-4 times per day. Ages 12 or older, 10 drops. Ages 12-2, 5 drops, or as prescribed with your doctor.

Uses

Temporarily supports your body when fighting the factors that lead to warts.*

*CLAIMS BASED ON TRADITIONAL HOMEOPATHIC PRACTICE, NOT ACCEPTED MEDICAL EVIDENCE. NOT FDA EVALUATED.

This product is not intended to diagnose, treat, cure, or prevent any disease.

Uses

Temporarily supports your body when fighting the factors that lead to warts.*

*CLAIMS BASED ON TRADITIONAL HOMEOPATHIC PRACTICE, NOT ACCEPTED MEDICAL EVIDENCE. NOT FDA EVALUATED.

This product is not intended to diagnose, treat, cure, or prevent any disease.

INACTIVE INGREDIENT

Ingredients

Inactive: Alcohol Base to Preserve Remedy

ACTIVE INGREDIENT

Active Ingredients: AnagallisD4+40C(Anagallis Arvensis), Anti CrudD10+100C(Antimonium Crudum), PenicillinumD20+200C(Penicillin), Sempervivum TectorumD7+70C(Houseleek), ThujaD4+40C(Thuja Occidentalis), X-RaysD20+200C(Rontgen Radiation)

KEEP OUT OF REACH OF CHILDREN

Warnings and Storage:

Ask a professional before use if pregnant or breastfeeding or if you have severe symptoms. Keep away from children. If you have a reaction to this product that is not positive, discontinue use. Store in a cool and dry place.

Warnings and Storage:

Ask a professional before use if pregnant or breastfeeding or if you have severe symptoms. Keep away from children. If you have a reaction to this product that is not positive, discontinue use. Store in a cool and dry place.

*CLAIMS BASED ON TRADITIONAL HOMEOPATHIC PRACTICE, NOT ACCEPTED MEDICAL EVIDENCE. NOT FDA EVALUATED.

This product is not intended to diagnose, treat, cure, or prevent any disease.

Entire package label